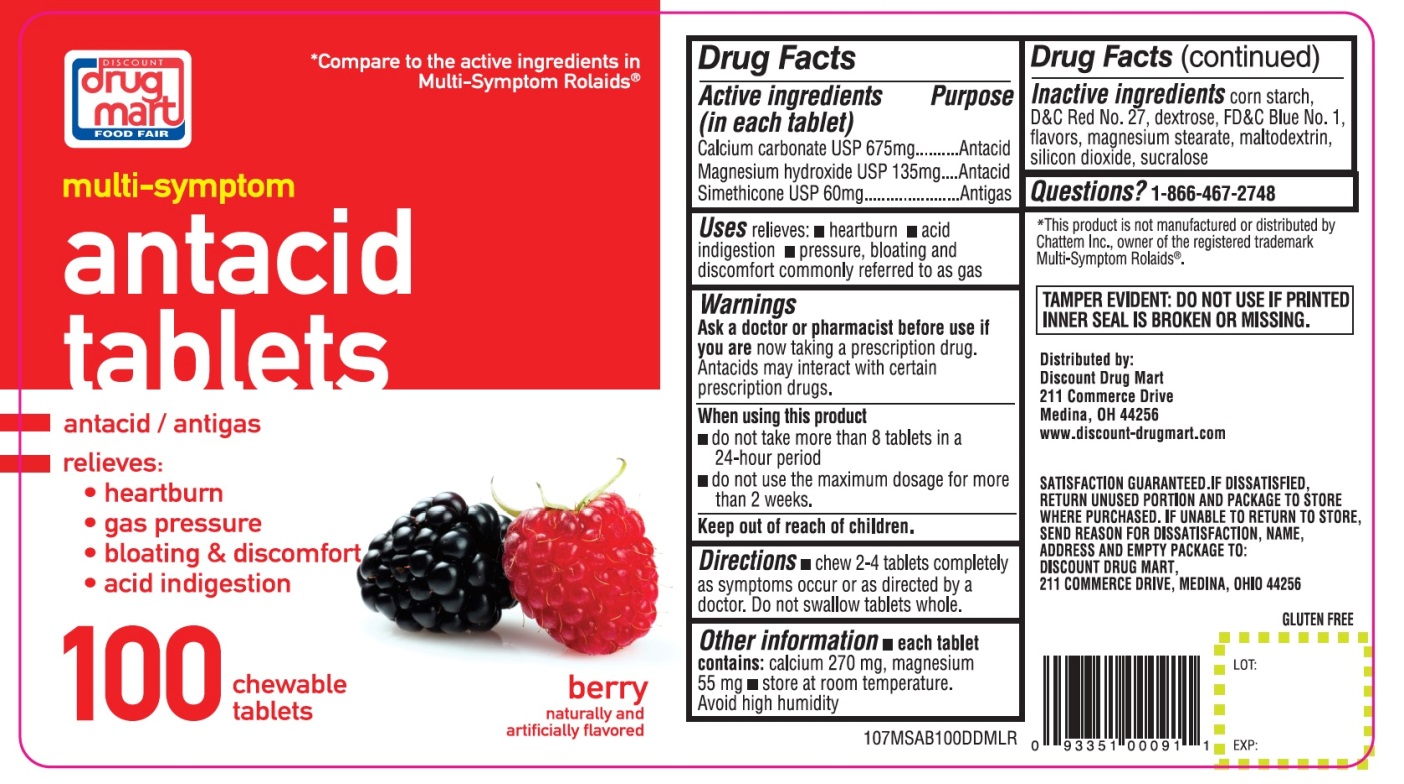 DRUG LABEL: Multi Symptom

NDC: 53943-107 | Form: TABLET, CHEWABLE
Manufacturer: DISCOUNT DRUG MART
Category: otc | Type: HUMAN OTC DRUG LABEL
Date: 20250911

ACTIVE INGREDIENTS: CALCIUM CARBONATE 675 mg/1 1; MAGNESIUM HYDROXIDE 135 mg/1 1; DIMETHICONE, UNSPECIFIED 60 mg/1 1
INACTIVE INGREDIENTS: STARCH, CORN; DEXTROSE, UNSPECIFIED FORM; FD&C BLUE NO. 1; D&C RED NO. 27; MAGNESIUM STEARATE; MALTODEXTRIN; SILICON DIOXIDE; SUCRALOSE

Multi Symptom antacid 100 Chewable Tablets Berry Flavor

Drug Facts

Active ingredients(in each tablet)

Calcium Carbonate USP 675 mg
Magnesium hydroxide USP 135 mg

Simethicone USP 60 mg

Purpose

Antacid

Antacid

Antigas

Uses

relieves:

- heartburn
- acid indigestion
- pressure, bloating and discomfort commonly referred to as gas

Warnings

Ask a doctor or pharmacist before use if you are

now taking a prescription drug. Antacids may interact with certain prescription drugs.

When using this product

- Do not take more than 8 tablets in a 24-hour period
- Do not use the maximum dosage for more than 2 weeks

Directions

- chew 2-4 tablets completely as symptoms occur or as directed by a doctor. Do not swallow tablets whole.

Other information

- each tablet contains:calcium 270 mg, magnesium 55 mg
- Store at room temperature. Avoid high humidity

Inactive ingredients

corn starch, D&C Red 27, dextrose, FD&C Blue No. 1, flavor, magnesium stearate, maltodextrin, silicon dioxide, sucralose.

PRINCIPAL DISPLAY PANEL

NDC# 53943-107-10

*Compare to the active ingredients in Multi-Symptoms Rolaids®

DISCOUNT drug mart

FOOD FAIR

multi-symptom

Antacid Tablets

Antacid/Antigas

Relieves:

- Heartburn
- Gas Pressure
- Bloating & Discomfort
- Acid Indigestion

100 Chewable Tablets

Berry

naturally and artificially flavored

GLUTEN-FREE

Distributed By: Discount Drug Mart

211 Commerce Drive,

Medina, Ohio 44256

www.discount-drugmart.com

TAMPER EVIDENT: DO NOT USE IF PRINTED INNSER SEAL IS BROKEN MISSING.

SATISFACTION GUARANTEED. IF DISSATISFIED, RETURN UNUSED PORTION AND PACKAGE TO STORE WHERE PURCHASED. IF UANBLE TO STORE SEND REASON FOR DISSATISFACTION, NAME, ADDRESS AND EMPTY PACKAGE TO: DISCOUNT DRUG MART, 211 COMMERCE DR., MEDINA, OHIO 44256

*This product is not manufactured or distributed by McNeil-PPC Inc., owner f the registered trademark ROLAIDS®.